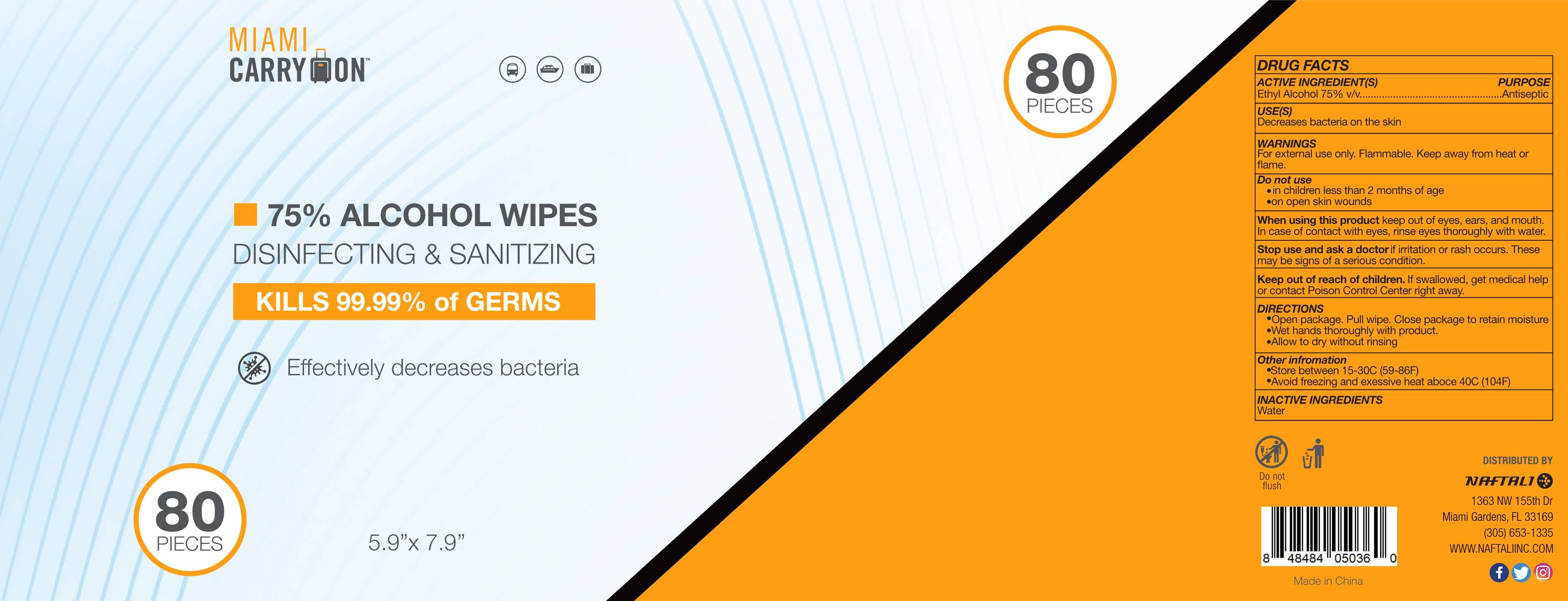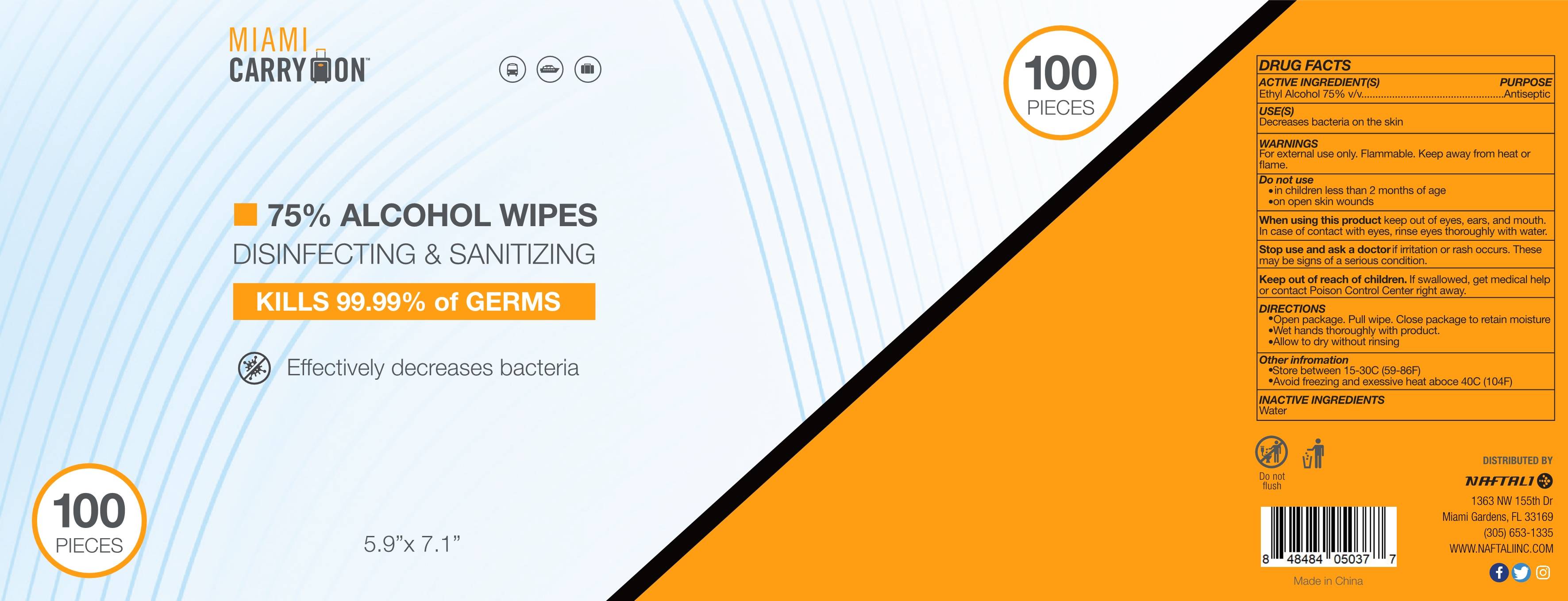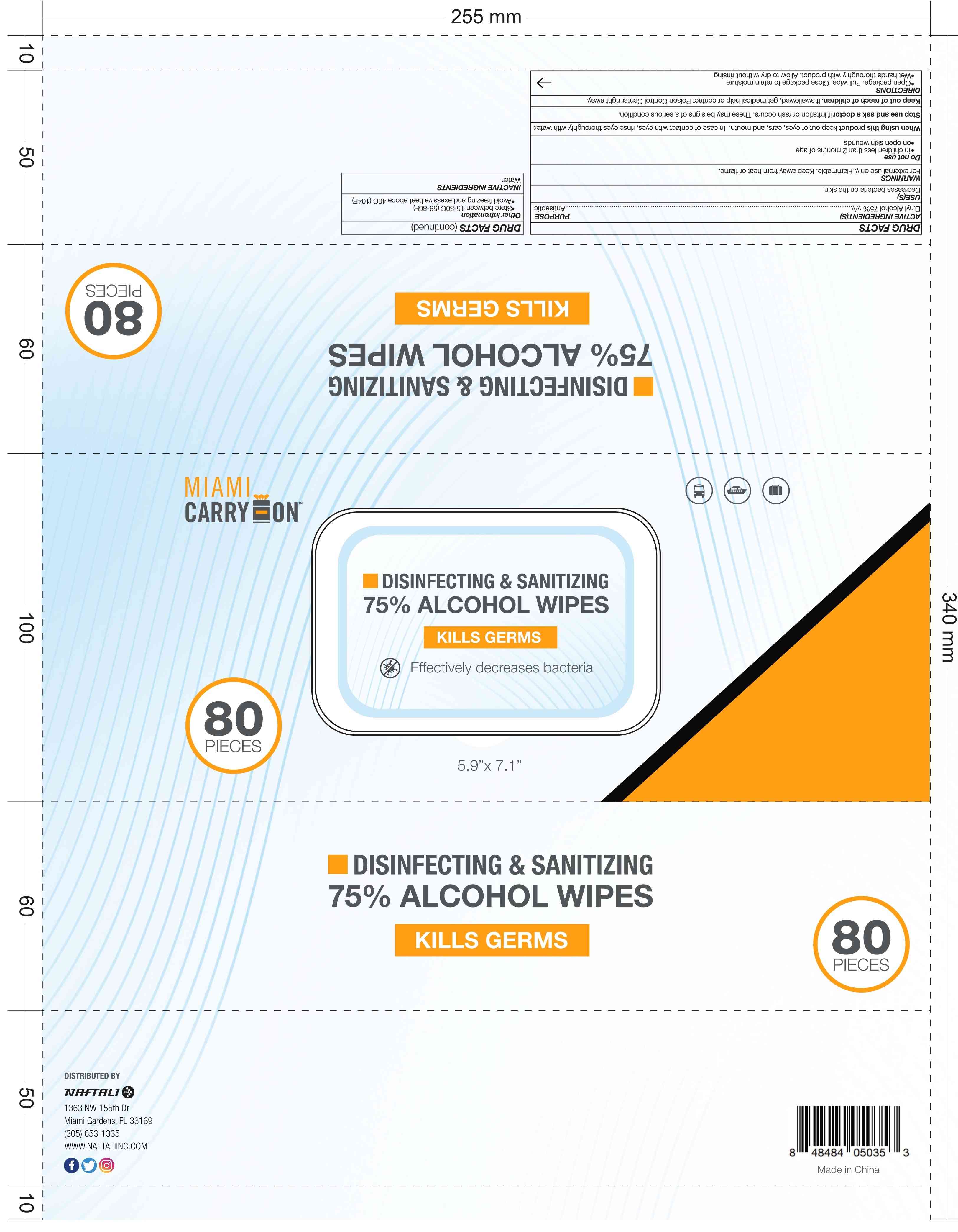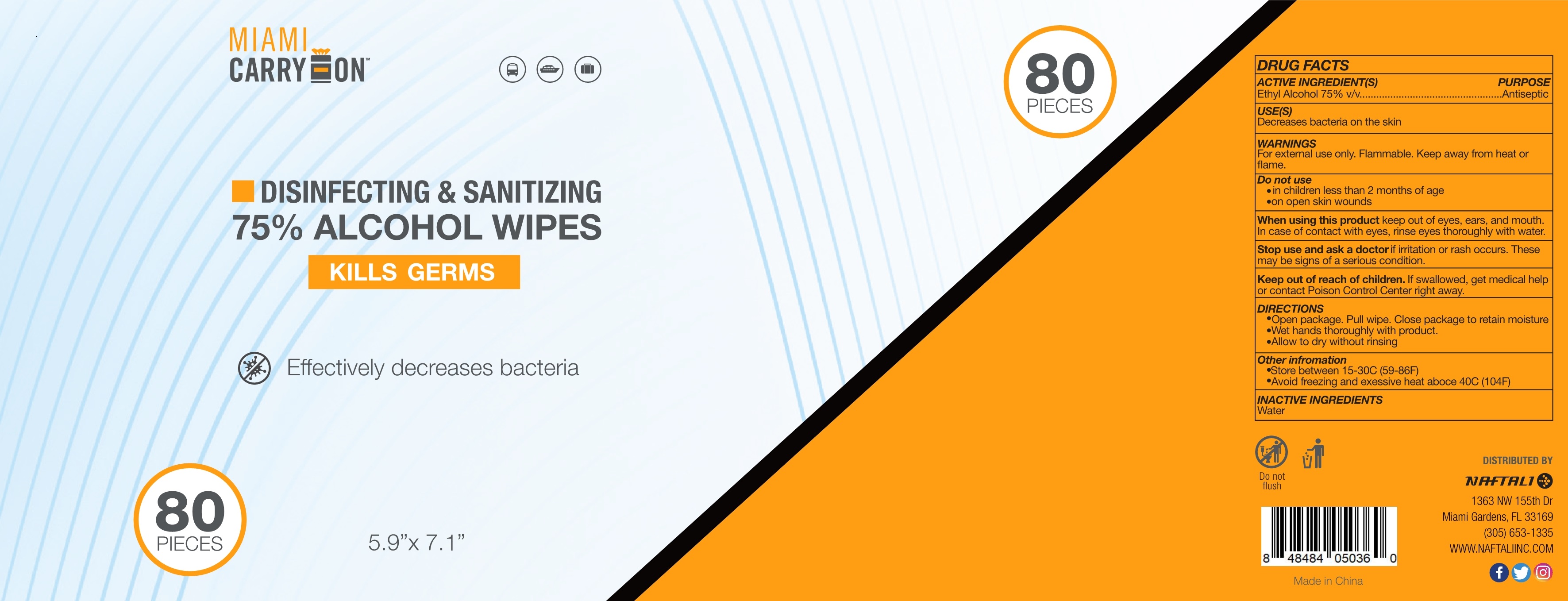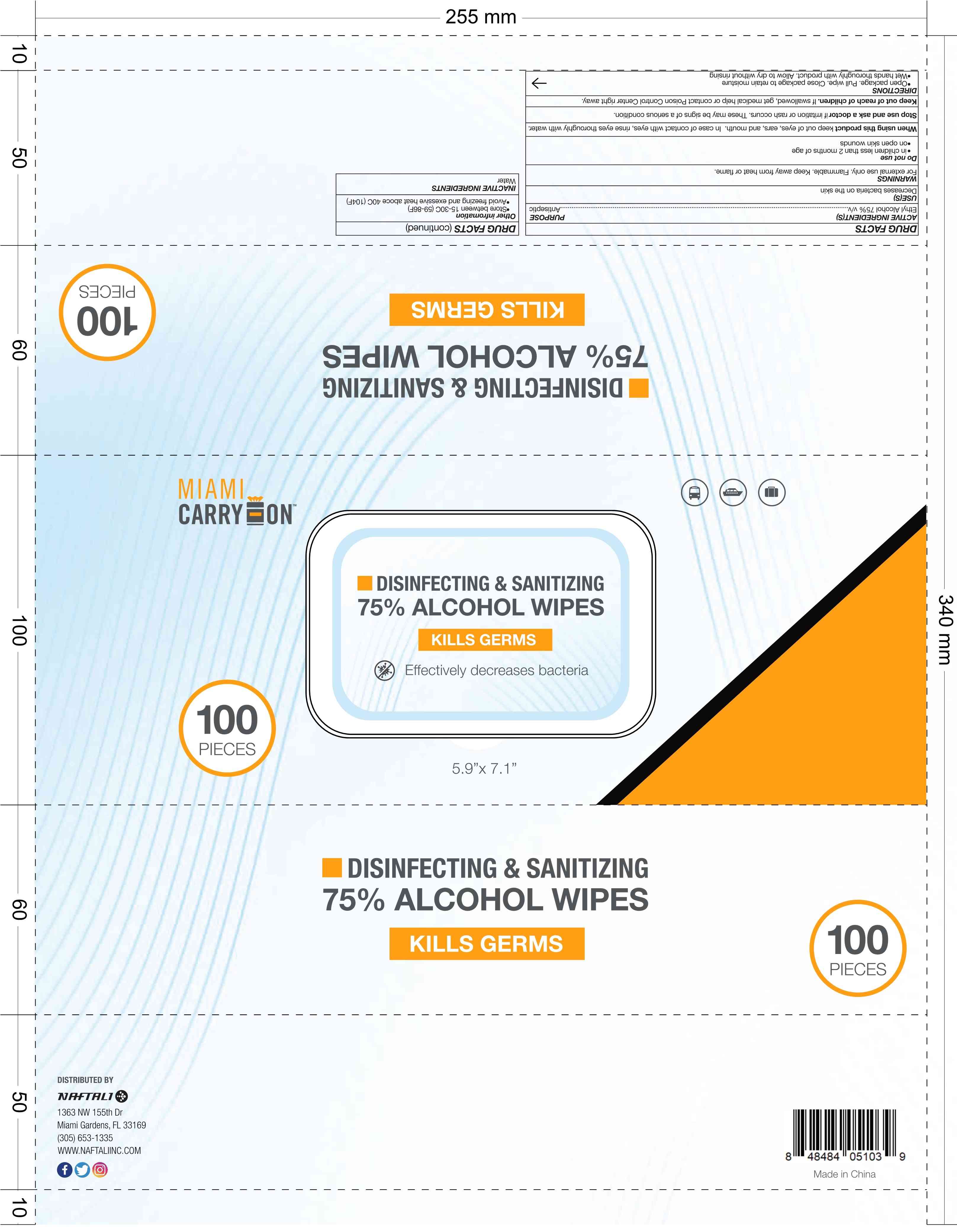 DRUG LABEL: 75% ALCOHOL WIPES
NDC: 74763-018 | Form: CLOTH
Manufacturer: ZHEJIANG GAFLE AUTO CHEMICAL CO.,LTD
Category: otc | Type: HUMAN OTC DRUG LABEL
Date: 20220328

ACTIVE INGREDIENTS: ALCOHOL 75 mL/100 1
INACTIVE INGREDIENTS: WATER

74763-018
75% ALCOHOL WIPES

ACTIVE INGERDIENT

Alcohol 75% by volume

PURPOSE

Antimicrobial

USES

Decreases bacteria on the skin

WARNINGS

For external use only. Flammable. Keep away from heat or flame.

Do not use
in children less than 2 months of age
on open skin wounds

When using this product keep out of eyes, ears, and mouth.
In case of contact with eyes, rinse eyes thoroughly with water.

Stop use and ask a doctor if irritation or rash occurs. These may be signs of a serious condition.

Keep out of reach of children. If swallowed, get medical help or contact Poison Control Center right away.

DO NOT USE

in children less than 2 months of age
on open skin wounds

When using this product keep out of eyes, ears, and mouth.
In case of contact with eyes, rinse eyes thoroughly with water.

Stop use and ask a doctor if irritation or rash occurs. These may be signs of a serious condition.

Keep out of reach of children. If swallowed, get medical help or contact Poison Control Center right away.

Stop use and ask a doctor if irritation or rash occurs. These may be signs of a serious condition.

Keep out of reach of children. If swallowed, get medical help or contact Poison Control Center right away.

DIRECTIONS

Open package. Pull wipe. Close package to retain moisture
Wet hands thoroughly with product.
Allow to dry without rinsing

OTHER INFORMATION

Store between 15-30C (59-86F)
Avoid freezing and exessive heat aboce 40C (104F)

INACTIVE INGERDIENTS

Water